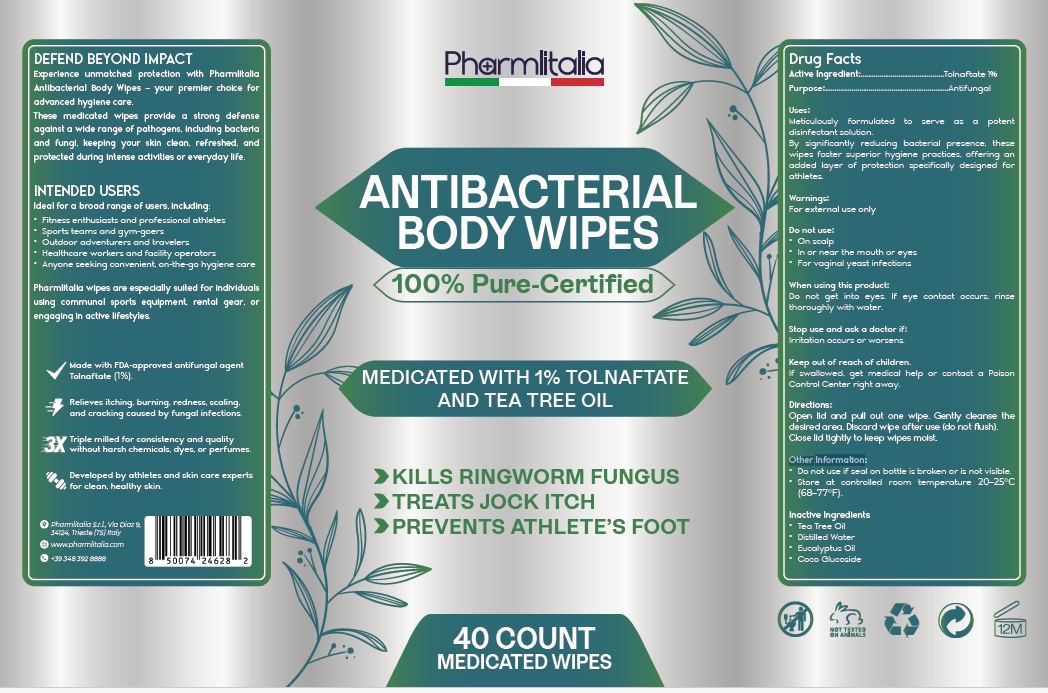 DRUG LABEL: Pharmlitalia Antifungal Medicated Body
NDC: 84938-010 | Form: CLOTH
Manufacturer: Foshan Sugar Max Cosmetics CO.,Ltd
Category: otc | Type: HUMAN OTC DRUG LABEL
Date: 20251110

ACTIVE INGREDIENTS: TOLNAFTATE 1 g/100 mL
INACTIVE INGREDIENTS: TEA TREE OIL; WATER; EUCALYPTUS OIL; COCO-GLUCOSIDE

Active ingredient

Tolnaftate 1%

Purpose

Antifungal

Uses

Meticulously formulated to serve as a potent disinfectant solution.
By significantly reducing bacterial presence, these wipes foster superior hygiene practices, offering an added layer of protection specifically designed for athletes.

Warnings

For external use only

Do not use:
• On scalp
• In or near the mouth or eyes
• For vaginal yeast infections

When using this product:
Do not get into eyes. If eye contact occurs, rinse thoroughly with water.

Stop use and ask a doctor if: irritation occurs or worsens.

Keep out of reach of children. If swallowed, get medical help or contact a Poison Control Center right away.

Directions

Open lid and pull out one wipe. Gently cleanse the desired area. Discard wipe after use (do not flush).
Close lid tightly to keep wipes moist.

Other Information

- Do not use if seal on bottle is broken or is not visible.
- Store at controlled room temperature 20–25°C (68–77°F).

Other Information

Tea Tree Oil, Distilled Water , Eucalyptus Oil, Coco Glucoside